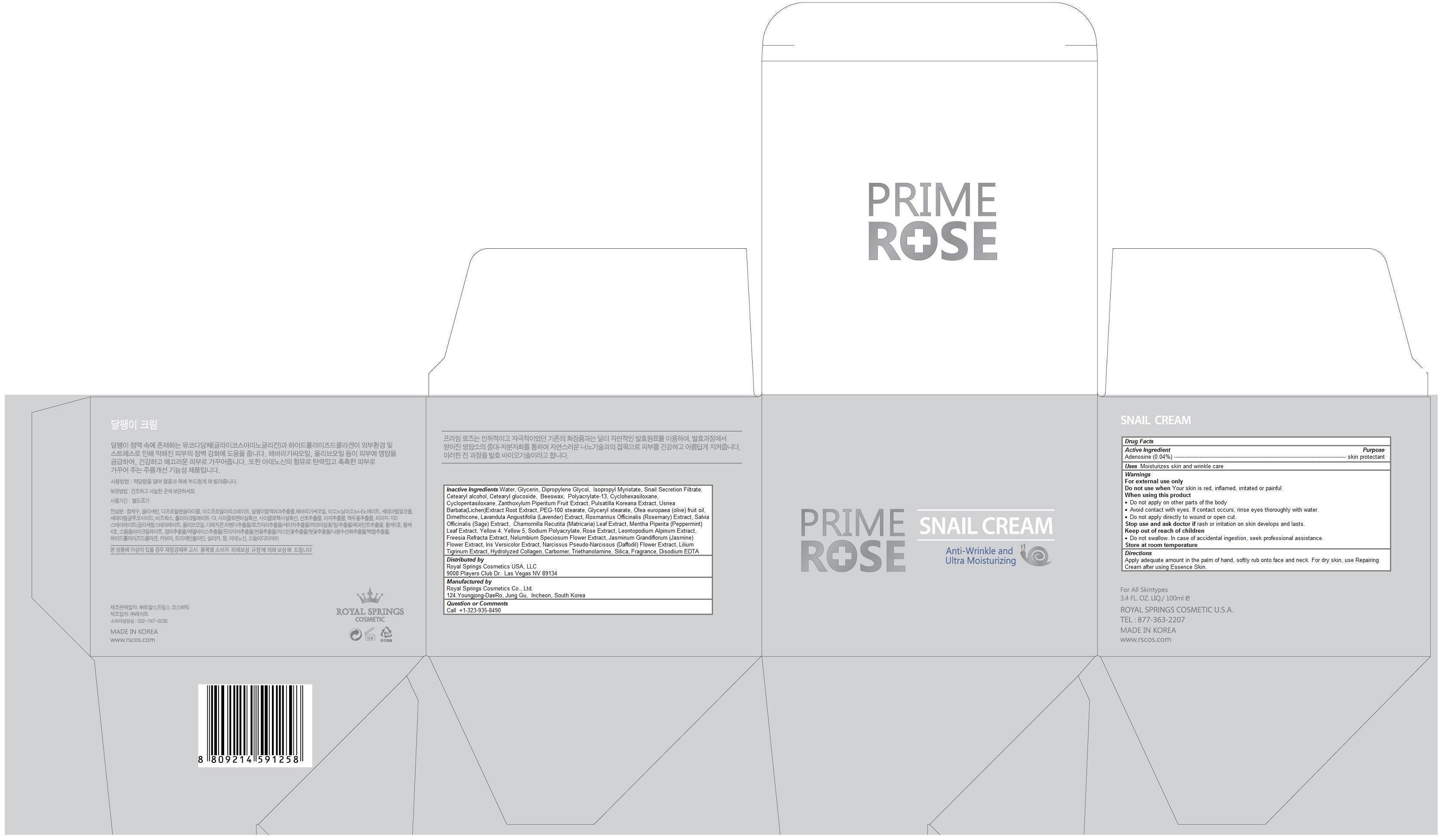 DRUG LABEL: PRIMEROSE SNAIL
NDC: 69888-101 | Form: CREAM
Manufacturer: Royal Springs Cosmetics USA, LLC
Category: otc | Type: HUMAN OTC DRUG LABEL
Date: 20190115

ACTIVE INGREDIENTS: ADENOSINE 0.0004 1/100 mL
INACTIVE INGREDIENTS: WATER; GLYCERIN; DIPROPYLENE GLYCOL; ISOPROPYL MYRISTATE; SNAIL, UNSPECIFIED; CETOSTEARYL ALCOHOL; CETEARYL GLUCOSIDE; YELLOW WAX; POLYESTER-8 (1400 MW, CYANODIPHENYLPROPENOYL CAPPED); CYCLOMETHICONE 6; CYCLOMETHICONE 5; ZANTHOXYLUM PIPERITUM FRUIT PULP; PULSATILLA KOREANA ROOT; USNEA BARBATA; PEG-100 STEARATE; GLYCERYL MONOSTEARATE; OLIVE OIL; DIMETHICONE; LAVANDULA ANGUSTIFOLIA FLOWERING TOP; ROSEMARY; SALVIA OFFICINALIS ROOT; MATRICARIA RECUTITA LEAF; MENTHA PIPERITA LEAF; FD&C YELLOW NO. 5; SODIUM POLYACRYLATE (2500000 MW); LEONTOPODIUM NIVALE SUBSP. ALPINUM ROOT; NELUMBO NUCIFERA FLOWER; JASMINUM GRANDIFLORUM FLOWER; NARCISSUS PSEUDONARCISSUS FLOWER; LILIUM LANCIFOLIUM BULB; CARBOMER HOMOPOLYMER TYPE C (ALLYL PENTAERYTHRITOL CROSSLINKED); TROLAMINE; SILICON DIOXIDE; EDETATE DISODIUM

PRIMEROSE SNAIL CREAM

Active ingredient

Adenosine (0.04%)

Purpose

skin protectant

Keep out of reach of children

- Do not swallow. In case of accidental ingestion, seek professional assistance.

Uses

Moisturizes skin and wrinkle care

Warnings

For external use only
Do not use when Your skin is red, inflamed, irritated or painful
When using this product
- Do not apply on other parts of the body
- Avoid contact with eyes. If contact occurs, rinse eyes thoroughly with water.
- Do not apply directly to wound or open cut.
Stop use and ask doctor if rash or irritation on skin develops and lasts.
Store at room temperature

Directions

Apply adequate amount in the palm of hand, softly rub onto face and neck. For dry skin, use Repairing Cream after using Essence Skin.

Inactive ingredients

Water, Glycerin, Dipropylene Glycol, Isopropyl Myristate, Snail Secretion Filtrate, Cetearyl alcohol, Cetearyl glucoside, Beeswax, Polyacrylate-13, Cyclohexasiloxane, Cyclopentasiloxane, Zanthoxylum Piperitum Fruit Extract, Pulsatilla Koreana Extract, Usnea Barbata(Lichen)Extract Root Extract, PEG-100 stearate, Glyceryl stearate, Olea europaea (olive) fruit oil, Dimethicone, Lavandula Angustifolia (Lavender) Extract, Rosmarinus Officinalis (Rosemary) Extract, Salvia Officinalis (Sage) Extract, Chamomilla Recutita (Matricaria) Leaf Extract, Mentha Piperita (Peppermint) Leaf Extract, Yellow 4, Yellow 5, Sodium Polyacrylate, Rose Extract, Leontopodium Alpinum Extract, Freesia Refracta Extract, Nelumbium Speciosum Flower Extract, Jasminum Grandiflorum (Jasmine) Flower Extract, Iris Versicolor Extract, Narcissus Pseudo-Narcissus (Daffodil) Flower Extract, Lilium Tigrinum Extract, Hydrolyzed Collagen, Carbomer, Triethanolamine, Silica, Fragrance, Disodium EDTA